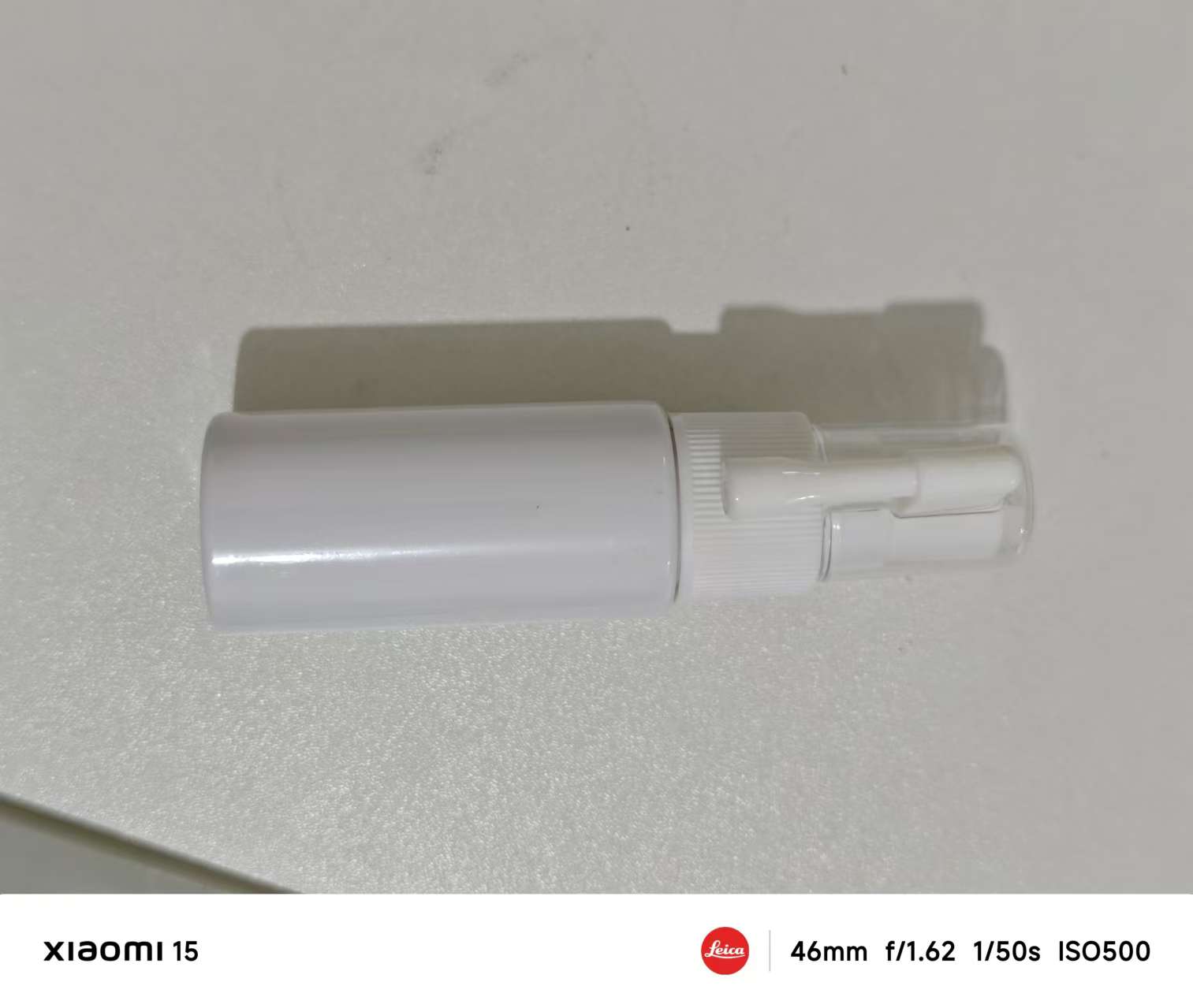 DRUG LABEL: Foot deodorant
NDC: 84727-004 | Form: PATCH
Manufacturer: Guangzhou Baishili Trading Co., Ltd
Category: otc | Type: HUMAN OTC DRUG LABEL
Date: 20241110

ACTIVE INGREDIENTS: CANDIDA ALBICANS 0.5 g/0.5 mL
INACTIVE INGREDIENTS: MENTHA PIPERITA 0.5 mL/0.5 mL

Health care function

Remove foot odor

Usage

Here are the general steps for using an athlete's foot spray:

Clean Your Feet: Before using the spray, thoroughly wash your feet with warm water, especially between the toes. Dry your feet well with a towel.

Apply Evenly: Shake the spray well and hold it about 10-15 cm away from your feet. Spray evenly on the affected areas, including between the toes. Avoid direct contact of the spray nozzle with the skin.

Let It Dry: After applying, allow your feet to air dry or gently pat them dry. Avoid putting on socks or shoes immediately to ensure full absorption.

Use Daily: Follow the product's instructions—usually, applying 1-2 times daily for several days will provide the best results.

Maintain Foot Hygiene: During treatment, keep your feet clean and dry, avoid wearing wet or non-breathable shoes, and wear clean socks to help prevent recurrence.

Be sure to read the product’s instructions carefully, and follow any specific recommendations to avoid overuse or skin irritation.

Matters needing attention

Here are some precautions for using athlete's foot spray:

Avoid Contact with Eyes and Mucous Membranes: Take care not to spray near the eyes, mouth, or other mucous membranes. If contact occurs, rinse thoroughly with water.

Keep Away from Flames: Many sprays contain flammable ingredients, so use them away from open flames or high heat to prevent accidental fire.

Perform a Patch Test: Before first use, apply a small amount on the wrist or inner arm to check for any irritation or allergic reaction. Discontinue use if discomfort occurs.

Do Not Apply on Broken Skin: If there are open wounds or severe infections, avoid spraying directly on the area to prevent pain or worsening infection.

Caution for Pregnant Women and Children: Pregnant or breastfeeding women and young children should consult a doctor before using the spray.

Proper Storage: Store the spray in a cool, dry place, out of the reach of children, and away from direct sunlight.

Complete the Recommended Course: Even if symptoms improve, continue using the spray for the full course as directed to prevent recurrence.

Following these precautions can help ensure safe and effective use of the athlete's foot spray.

Unsuitable people

Caution for Pregnant Women and Children: Pregnant or breastfeeding women and young children should consult a doctor before using the spray.

Keep out of reach of children.

Proper Storage: Store the spray in a cool, dry place, out of the reach of children, and away from direct sunlight.

DOSAGE & ADMINISTRATION SECTION

Complete the Recommended Course: Even if symptoms improve, continue using the spray for the full course as directed to prevent recurrence.

INACTIVE INGREDIENT SECTION

Mentha Piperita

DOSAGE & ADMINISTRATION SECTION

Candida Albicans